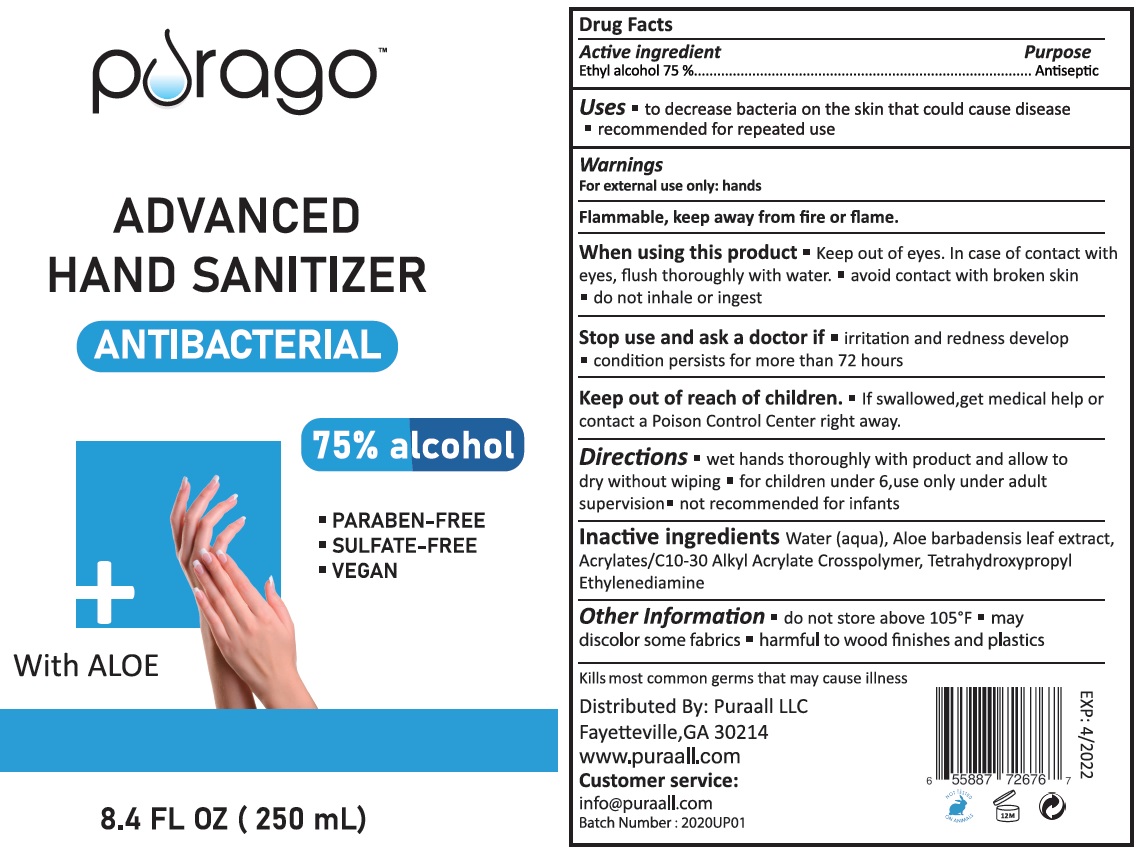 DRUG LABEL: Purago Hand Sanitizer
NDC: 76812-009 | Form: GEL
Manufacturer: Puraall LLC
Category: otc | Type: HUMAN OTC DRUG LABEL
Date: 20200602

ACTIVE INGREDIENTS: ALCOHOL 0.75 mL/1 mL
INACTIVE INGREDIENTS: WATER; ALOE VERA LEAF; EDETOL

Purago Hand Sanitizer with Aloe

Active ingredient

Ethyl alcohol 75%

Purpose

Antiseptic

Uses

- to decrease bacteria on the skin that could cause disease
- recommended for repeated use

Warnings

For external use only: hands

Flammable, keep away from fire or flame.

When using this product

- Keep out of eyes. In case of contact with eyes, flush thoroughly with water.
- avoid contact with broken skin
- do not inhale or ingest

Stop use and ask a doctor if

- irritation and redness develop
- condition persist for more than 72 hours

Keep out of reach of children.

If swallowed, get medical help or contact a Poison Control Center right away.

Directions

- wet hands thoroughly with product and allow to dry without wiping
- for children under 6, use only under adult supervision
- not recommended for infants

Inactive ingredients

Water, Aloe Barbadensis Leaf Extract, Acrylate/C10-30 alkyl Acrylate Crosspolymer, Tetrahydroxypropyl Ethylenediamine

Other Information

- do not store above 105°F
- may discolor some fabrics
- harmful to wood finishes and plastics